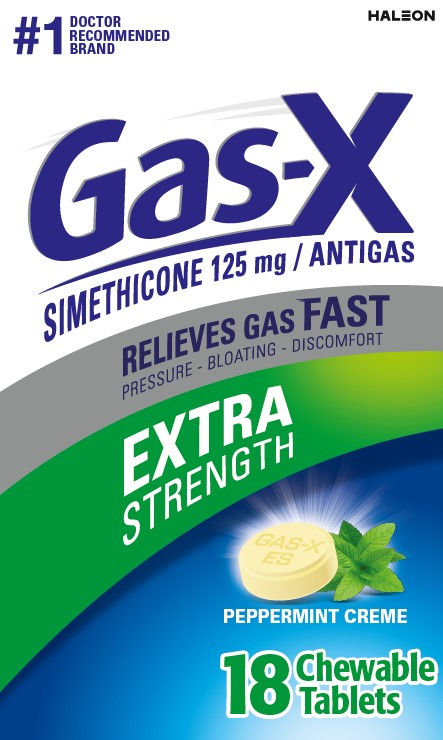 DRUG LABEL: Gas-X
NDC: 0067-0129 | Form: TABLET, CHEWABLE
Manufacturer: Haleon US Holdings LLC
Category: otc | Type: HUMAN OTC DRUG LABEL
Date: 20250226

ACTIVE INGREDIENTS: DIMETHICONE, UNSPECIFIED 125 mg/1 1
INACTIVE INGREDIENTS: TRIBASIC CALCIUM PHOSPHATE; SILICON DIOXIDE; CORN SYRUP; D&C RED NO. 30 ALUMINUM LAKE; D&C YELLOW NO. 10 ALUMINUM LAKE; DEXTROSE, UNSPECIFIED FORM; BUTTER; MALTODEXTRIN; MODIFIED CORN STARCH (1-OCTENYL SUCCINIC ANHYDRIDE)

Drug Facts

Active ingredient (in each tablet)

Simethicone 125 mg

Purpose

Antigas

Uses

for the relief of

- pressure, bloating, and fullness commonly referred to as gas

Directions

- adults and children 12 years and older: chew 1 or 2 tablets as needed after meals and at bedtime. Chew or crush tablets completely before swallowing.
- do not exceed 4 tablets in 24 hours except under the advice and supervision of a physician

Other information

- each chewable tablet contains: calcium 45 mg
- store at controlled room temperature 20-25°C (68-77°F)
- protect from moisture

Inactive ingredients

calcium phosphate tribasic, colloidal silicon dioxide, corn syrup solids, D&C red no. 30 aluminum lake, D&C yellow no. 10 aluminum lake, dextrose, flavors, lipolyzed butteroil, maltodextrin, modified corn starch

Questions or comments?

1-855-328-5204

Generic Section

Gas-X Extra Strength Tablets offer fast, effective relief of pressure and bloating that antacids can’t provide. They are specially formulated with simethicone, the antigas medicine doctors recommend most for pressure, bloating or discomfort referred to as gas.

READ ALL PRODUCT INFORMATION BEFORE USING. KEEP CARTON FOR IMPORTANT INFORMATION.

TAMPER EVIDENT FEATURE: Gas-X tablets are sealed in blister backets. Use only if the individual seal is unbroken.

Gas-X Extra Strength Peppermint Crème chewable tablets have a pleasantly smooth, creamy mint flavor. Chewable tablets are also available in a great tasting Cherry Creme flavor.

Principal Display Panel

#1 DOCTOR RECOMMENDED BRAND

GAS-X

SIMETHICONE 125 mg / ANTIGAS

RELIEVES GAS FAST

PRESSURE – BLOATING – DISCOMFORT

EXTRA STRENGTH

PEPPERMINT CREME

18 Chewable Tablets